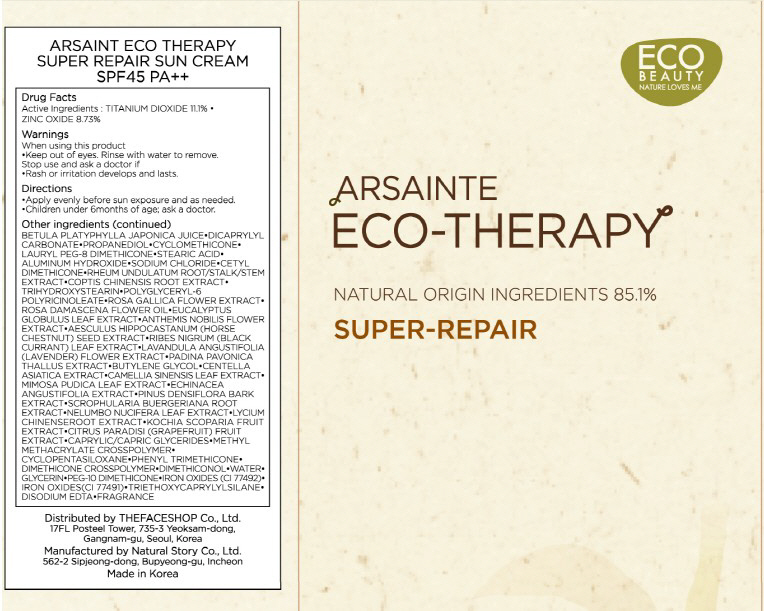 DRUG LABEL: ARSAINTE ECO THERAPY SUPER REPAIR SUN
NDC: 51523-002 | Form: CREAM
Manufacturer: THEFACESHOP CO., LTD.
Category: otc | Type: HUMAN OTC DRUG LABEL
Date: 20100712

ACTIVE INGREDIENTS: TITANIUM DIOXIDE 5.55 mL/50 mL; ZINC OXIDE 4.36 mL/50 mL

Drug Facts

Active Ingredients: TITANIUM DIOXIDE, ZINC OXIDE

Inactive Ingredients:

BETULA PLATYPHYLLA JAPONICA JUICE, DICAPRYLYL CARBONATE, PROPANEDIOL, CYCLOMETHICONE, LAURYL PEG-8 DIMETHICONE, STEARIC ACID, ALUMINUM HYDROXIDE,
SODIUM CHLORIDE, CETYL DIMETHICONE, RHEUM UNDULATUM ROOT/STALK/STEM EXTRACT, COPTIS CHINENSIS ROOT EXTRACT, TRIHYDROXYSTEARIN, POLYGLYCERYL-6 POLYRICINOLEATE,
ROSA GALLICA FLOWER EXTRACT, ROSA DAMASCENA FLOWER OIL, EUCALYPTUS GLOBULUS LEAF EXTRACT, ANTHEMIS NOBILIS FLOWER EXTRACT, AESCULUS HIPPOCASTANUM (HORSE CHESTNUT) SEED EXTRACT,
RIBES NIGRUM (BLACK CURRANT) LEAF EXTRACT, LAVANDULA ANGUSTIFOLIA (LAVENDER) FLOWER EXTRACT, PADINA PAVONICA THALLUS EXTRACT, BUTYLENE GLYCOL,
CENTELLA ASIATICA EXTRACT, CAMELLIA SINENSIS LEAF EXTRACT, MIMOSA PUDICA LEAF EXTRACT, ECHINACEA ANGUSTIFOLIA EXTRACT, PINUS DENSIFLORA BARK EXTRACT,
SCROPHULARIA BUERGERIANA ROOT EXTRACT, NELUMBO NUCIFERA LEAF EXTRACT, LYCIUM CHINENSE ROOT EXTRACT, KOCHIA SCOPARIA FRUIT EXTRACT,
CITRUS PARADISI (GRAPEFRUIT) FRUIT EXTRACT, CAPRYLIC/CAPRIC GLYCERIDES, METHYL METHACRYLATE CROSSPOLYMER, CYCLOPENTASILOXANE, PHENYL TRIMETHICONE,
DIMETHICONE CROSSPOLYMER, DIMETHICONOL, WATER, GLYCERIN, PEG-10 DIMETHICONE, IRON OXIDES(CI 77492), IRON OXIDES(CI 77491), TRIETHOXYCAPRYLYLSILANE,
DISODIUM EDTA, FRAGRANCE

Warnings:
When using this product
Keep out of eyes. Rinse with water to remove.
Stop use and ask a doctor if
Rash or irritation develops and lasts.
Directions:
Apply evenly before sun exposure and as needed.
Children under 6months of age; ask a doctor.